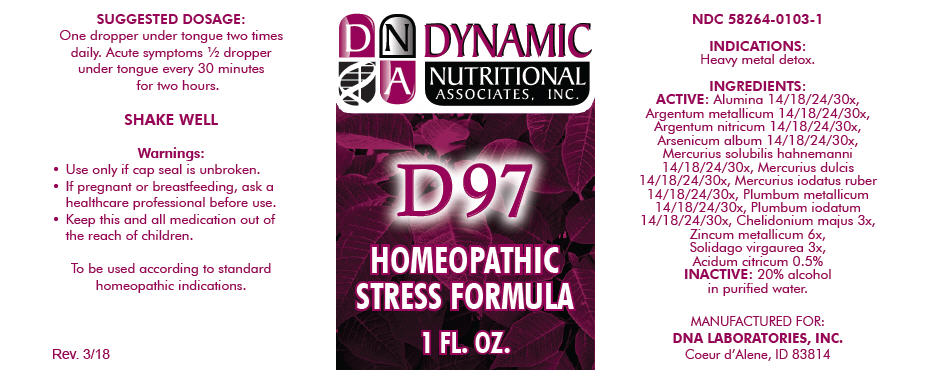 DRUG LABEL: D-97
NDC: 58264-0103 | Form: SOLUTION
Manufacturer: DNA Labs, Inc.
Category: homeopathic | Type: HUMAN OTC DRUG LABEL
Date: 20250113

ACTIVE INGREDIENTS: MERCURIUS SOLUBILIS 14 [hp_X]/1 mL; CALOMEL 14 [hp_X]/1 mL; MERCURIC IODIDE 14 [hp_X]/1 mL; LEAD 14 [hp_X]/1 mL; LEAD IODIDE 14 [hp_X]/1 mL; CHELIDONIUM MAJUS 3 [hp_X]/1 mL; ZINC 6 [hp_X]/1 mL; SOLIDAGO VIRGAUREA FLOWERING TOP 3 [hp_X]/1 mL; CITRIC ACID MONOHYDRATE 2 [hp_X]/1 mL; ALUMINUM OXIDE 14 [hp_X]/1 mL; SILVER 14 [hp_X]/1 mL; SILVER NITRATE 14 [hp_X]/1 mL; ARSENIC TRIOXIDE 14 [hp_X]/1 mL
INACTIVE INGREDIENTS: ALCOHOL; WATER

D-97

NDC 58264-0103-1

INDICATIONS

PURPOSE

Heavy metal detox.

INGREDIENTS

ACTIVE

Alumina 14/18/24/30x, Argentum metallicum 14/18/24/30x, Argentum nitricum 14/18/24/30x, Arsenicum album 14/18/24/30x, Mercurius solubilis hahnemanni 14/18/24/30x, Mercurius dulcis 14/18/24/30x, Mercurius iodatus ruber 14/18/24/30x, Plumbum metallicum 14/18/24/30x, Plumbum iodatum 14/18/24/30x, Chelidonium majus 3x, Zincum metallicum 6x, Solidago virgaurea 3x, Acidum citricum 0.5%

INACTIVE

20% alcohol in purified water.

SUGGESTED DOSAGE

One dropper under tongue two times daily. Acute symptoms ½ dropper under tongue every 30 minutes for two hours.

STORAGE AND HANDLING

SHAKE WELL

Warnings

- Use only if cap seal is unbroken.

PREGNANCY OR BREAST FEEDING

- If pregnant or breastfeeding, ask a healthcare professional before use.

KEEP OUT OF REACH OF CHILDREN

- Keep this and all medication out of the reach of children.

To be used according to standard homeopathic indications.

PRINCIPAL DISPLAY PANEL - 1 FL. OZ. Bottle Label

DYNAMIC
NUTRITIONAL
ASSOCIATES, INC.

D 97

HOMEOPATHIC
STRESS FORMULA

1 FL. OZ.